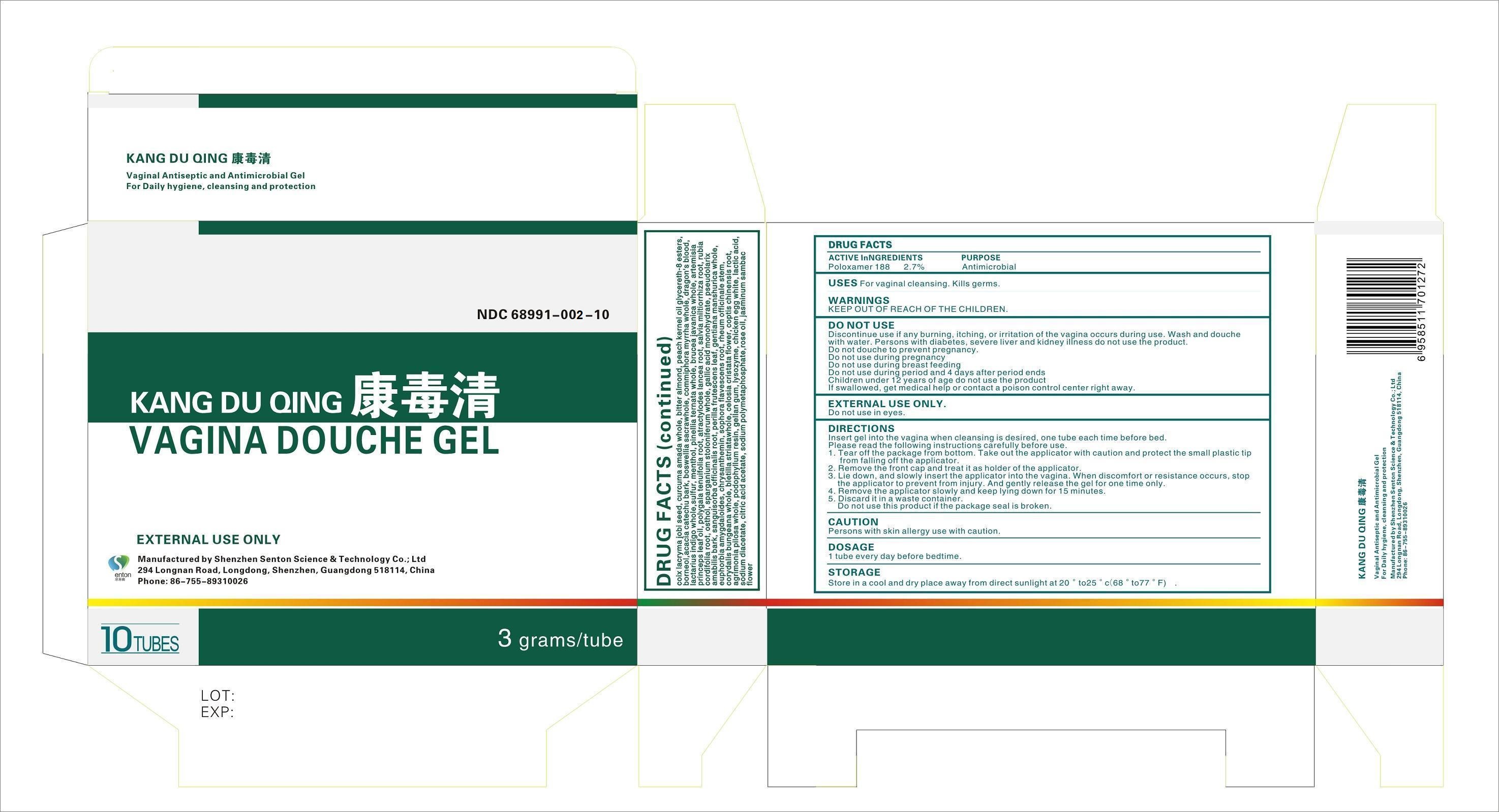 DRUG LABEL: Mayer /Kang Du Qing Cybercy
NDC: 68991-002 | Form: GEL
Manufacturer: Shenzhen Senton Science & Technology Co. Ltd
Category: otc | Type: HUMAN OTC DRUG LABEL
Date: 20241213

ACTIVE INGREDIENTS: POLOXAMER 188 2.7 g/100 g
INACTIVE INGREDIENTS: COIX LACRYMA-JOBI SEED; CURCUMA AMADA WHOLE; BITTER ALMOND; PEACH KERNEL OIL GLYCERETH-8 ESTERS; BORNEOL; ACACIA CATECHU BARK; BOSWELLIA SACRA WHOLE; COMMIPHORA MYRRHA WHOLE; DRAGON'S BLOOD; LACTARIUS INDIGO WHOLE; SULFUR; MENTHOL; PINELLIA TERNATA WHOLE; BRUCEA JAVANICA WHOLE; ARTEMISIA PRINCEPS LEAF OIL; POLYGALA TENUIFOLIA ROOT; ATRACTYLODES LANCEA ROOT; SALVIA MILTIORRHIZA ROOT; RUBIA CORDIFOLIA ROOT; OSTHOL; SPARGANIUM STOLONIFERUM WHOLE; GALLIC ACID MONOHYDRATE; PSEUDOLARIX AMABILIS BARK; SANGUISORBA OFFICINALIS ROOT; PERILLA FRUTESCENS LEAF; GENTIANA MANSHURICA WHOLE; EUPHORBIA AMYGDALOIDES; CHRYSANTHEMIN; SOPHORA FLAVESCENS ROOT; RHEUM OFFICINALE STEM; CORYDALIS BUNGEANA WHOLE; BLETILLA STRIATA WHOLE; CELOSIA CRISTATA FLOWER; COPTIS CHINENSIS ROOT; AGRIMONIA PILOSA WHOLE; PODOPHYLLUM RESIN; GELLAN GUM (LOW ACYL); LYSOZYME, CHICKEN EGG WHITE; LACTIC ACID; SODIUM DIACETATE; CITRIC ACID ACETATE; SODIUM POLYMETAPHOSPHATE; ROSE OIL; JASMINUM SAMBAC FLOWER

Shenzhen Senton Science & Technology Co. Ltd

ACTIVE INGREDIENTS

POLOXAMER 188 2.7%

PURPOSES

Antimicrobial

USES

For Vaginal Cleansing. Kills Germs.

WARNINGS:

Keep out of reach of children.

WARNINGS:

Discontinue use if any burning, itching, or irritation of the vagina occurs during use.

Wash and douche with water.

Do not douche to prevent pregnancy.

During pregnancy.

Do not use during breast feeding.

Do not use during period and 4 days after period ends.

Children under 12 years of age do not use the product.

If swallowed, get medical help or contact a poison control center right away.

FOR EXTERNAL USE ONLY.

Do not use in eyes.

DIRECTIONS:

Insert the gel into the vagina when cleansing is desired, one tube each time before bed.

Please read the following instructions carefully before use.

1. Take off the package from bottom. Take out the applicator with caution and protect the small plastic tip from falling off the applicator.

2. Remove the the front cap and treat it as holder of the applicator.

3. Lie down and slowly insert the applicator into the vagina. When discomfort or resistance occurs, stops the applicator to prevent from injury. And gently release the gel for one time only.

4. Remove the applicator slowly and keep lying down for 15 minutes.

5. Discard it in a waste container.

Do not use this product if the package seal is broken.

CAUTION:

Persons with skin allergy use with caution.

DOSAGE

1 tube every day before bedtime

STORAGE

Store in a cool and dry place away from direct sunlight at 20 - 25 degrees Centigrade or 68 - 77 degrees Fahrenheit.

INACTIVE INGREDIENTS

COIX LACRYMA JOBI SEED, CURCUMA AMADA WHOLE, BITTER ALMOND, PEACH KERNEL OIL GLYCERETH-8 ESTERS, BORNEOL, ACACIA CATECHU BARK, BOSWELLIA SACRA WHOLE, COMMIPHORA MYRRHA WHOLE, DRAGON'S BLOOD, LACTARIUS INDIGO WHOLE,SULFUR, MENTHOL, PINELLIA TERNATA WHOLE, BRUCEA JAVANICA WHOLE, ARTEMISIA PRINCEPS LEAF OIL, POLYGALA TENUIFOLIA ROOT, ATRACTYLODES LANCEA ROOT, SALVIA MILTIORRHIZA ROOT, RUBIA CORDIFOLIA ROOT, OSTHOL, SPARGANIUM STOLONIFERUM WHOLE, GALLIC ACID MONOHYDRATE, PSEUDOLARIX AMABILIS BARK, SANGUISORBA OFFICINALIS ROOT, PERILLA FRUTESCENS LEAF, GENTIANA MANSHURICA WHOLE, EUPHORBIA AMYGDALOIDES, CHRYSANTHEMIN, SOPHORA FLAVESCENS ROOT, RHEUM OFFICINALE STEM, CORYDALIS BUNGEANA WHOLE, BLETILLA STRIATA WHOLE, CELOSIA CRISTATA FLOWER, COPTIS CHINENSIS ROOT, AGRIMONIA PILOSA WHOLE, PODOPHYLLUM RESIN, GELLAN GUM, LYSOZYME, CHICKEN EGG WHITE, LACTIC ACID, SODIUM DIACETATE, CITRIC ACID ACETATE, SODIUM POLYMETAPHOSPHATE, ROSE OIL, JASMINUM SAMBAC FLOWER